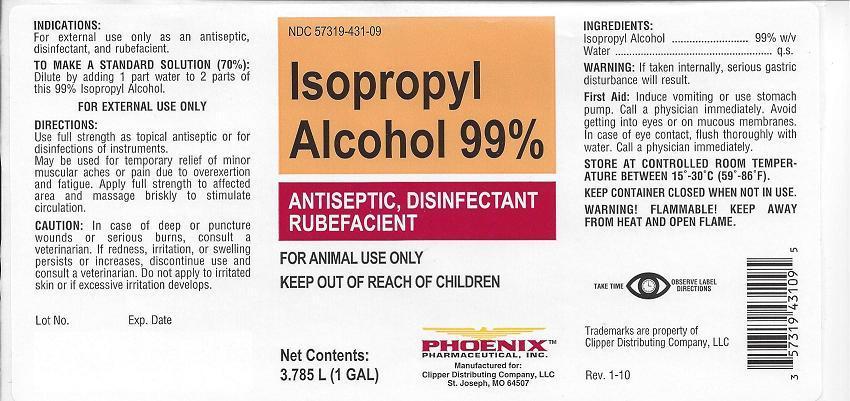 DRUG LABEL: Isopropyl Alcohol
NDC: 57319-431 | Form: LIQUID
Manufacturer: Phoenix Pharmaceutical Inc./ Clipper Distributing, Inc.
Category: animal | Type: OTC ANIMAL DRUG LABEL
Date: 20130917

ACTIVE INGREDIENTS: ISOPROPYL ALCOHOL 99 mL/100 mL
INACTIVE INGREDIENTS: WATER

Isopropyl Alcohol 99%

NDC 57319-431-09 Isopropyl Alcohol 99% ANTISEPTIC, DISINFECTANT RUBEFACIENT

FOR ANIMAL USE ONLY

KEEP OUT OF REACH OF CHILDREN

Net Contents:

3.785 L (1 GAL)

PHOENIX

PHARMACEUTICAL, INC.

Manufactured for:

Clipper Distributing Company, LLC

St. Joseph, MO 64507

INDICATIONS:

For external use only as an antiseptic, disinfectant, and rubefacient.

TO MAKE A STANDARD SOLUTION (70%):

Dilute by adding 1 part water to 2 parts of this 99% Isopropyl Alcohol.

DIRECTIONS:

Use full strength as topical antiseptic or for disinfections of instruments.

May be used for temporary relief of minor muscular aches or pain due to overexertion and fatigue. Apply full strength to affected area and massage briskly to stimulate circulation.

CAUTION:

In case of deep or puncture wounds or serious burns, consult a veterinarian. If redness, irritation, or swelling persists or increases, discontinue use and consult a veterinarian. Do not apply to irritated skin or if excessive irritation develops.

INGREDIENTS:

Isopropyl Alcohol ........... 99% w/v
Water ............................. q.s.

WARNING:

If taken internally, serious gastric disturbance will result.

First Aid:

Induce vomiting or use stomach pump. Call a physician immediately. Avoid getting into eyes or on mucous membranes. In case of eye contact, flush thoroughly with water. Call a physician immediately.

STORE AT CONTROLLED ROOM TEMPERATURE BETWEEN 15°-30°C (59°-86°F).

KEEP CONTAINER CLOSED WHEN NOT IN USE.

WARNING! FLAMMABLE! KEEP AWAY FROM HEAT AND OPEN FLAME.

TAKE TIME OBSERVE LABEL DIRECTIONS

Trademarks are property of
Clipper Distributing Company, LLC

Rev 1-10